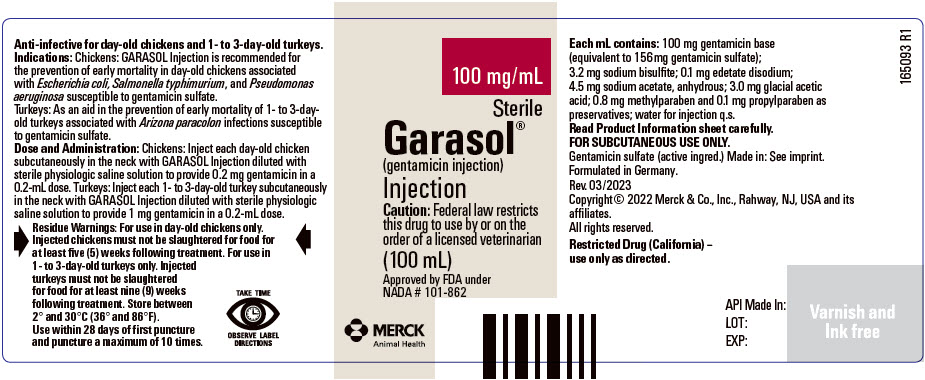 DRUG LABEL: GARASOL
NDC: 0061-0134 | Form: INJECTION, SOLUTION
Manufacturer: Merck Sharp & Dohme Corp.
Category: animal | Type: OTC ANIMAL DRUG LABEL
Date: 20260206

ACTIVE INGREDIENTS: GENTAMICIN SULFATE 100 mg/1 mL

Garasol®
(gentamicin injection)

Injection – 100 mg/mL
Anti-Infective for
Day-Old Chickens and
One- to Three-Day-Old
Turkeys

PRODUCT
INFORMATION

Approved by FDA under NADA # 101-862

CAUTION Federal law restricts this drug to use by or on the order of a licensed veterinarian

DESCRIPTION

DESCRIPTION Each milliliter of GARASOL Injection contains 100 mg gentamicin base (equivalent to 156 mg gentamicin sulfate); 3.2 mg sodium bisulfite; 0.1 mg edetate disodium; 4.5 mg sodium acetate, anhydrous; 3.0 mg glacial acetic acid; 0.8 mg methylparaben and 0.1 mg propylparaben as preservatives; water for injection q.s.

CHEMISTRY Gentamicin is a bactericidal aminoglycoside antibiotic derived from Micromonospora purpurea of the Actinomycetes group. It is a powder, readily soluble in water and basic in nature. Gentamicin aqueous solutions do not require refrigeration and are stable overa wide range of temperatures and pH.

VETERINARY INDICATIONS

INDICATIONS Day-old chickens – GARASOL Injection is recommended for the prevention of early mortality associated with Escherichia coli, Salmonella typhimurium, and Pseudomonas aeruginosa susceptible to gentamicin sulfate. Turkeys – As an aid in the prevention of early mortality of 1- to 3-day-old turkeys associated with Arizona paracolon infections susceptible to gentamicin sulfate.

DOSAGE AND ADMINISTRATION

Chickens: Each day-old chicken should be aseptically injected subcutaneously in the neck with GARASOL Injection diluted with sterile, physiologic saline solution to provide 0.2 mg gentamicin in a 0.2-mL dose. This concentration can be provided by diluting GARASOL Injection as follows:

GARASOL mL | Sterile Saline mL | # Doses | Dose/Chicken mL
1 | 99 | 500 | 0.2
2 | 198 | 1000 | 0.2
4 | 396 | 2000 | 0.2
10 | 990 | 5000 | 0.2
100 (1 bottle) | 9900 | 50000 | 0.2

Turkeys: Each 1- to 3-day-old turkey should be aseptically injected subcutaneously in the neck with GARASOL Injection diluted with sterile, physiologic saline solution to provide 1 mg gentamicin in a 0.2-mL dose. The dose should be injected under the loose skin on top of the neck, halfway between the head and base of the neck. This concentration can be provided by diluting GARASOL Injection as follows:

GARASOL mL | Sterile Saline mL | # Doses | Dose/Turkey mL
1 | 19 | 100 | 0.2
2 | 38 | 200 | 0.2
4 | 76 | 400 | 0.2
10 | 190 | 1000 | 0.2
100 (1 bottle) | 1900 | 10000 | 0.2

Clean and sterilize needles and syringes by boiling in water for 15 minutes prior to use.

Disinfect the injection site and top of the bottle with a suitable disinfectant, such as 70% isopropyl alcohol.

Use all precautions to prevent contamination of vial contents.

RESIDUE WARNING

Residue Warnings For use in day-old chickens and 1- to 3-day-old turkeys only. Chickens injected with GARASOL Injection must not be slaughtered for food for at least 5 weeks following treatment. Turkeys injected with GARASOL Injection must not be slaughtered for food for at least 9 weeks following treatment.

HOW SUPPLIED

HOW SUPPLIED GARASOL Injection, 100 mg/mL, is available in 100-mL multiple-dose vials, NDC 0061-0134-01.

STORAGE AND HANDLING

Store between 2° and 30°C (36° and 86°F). Use within 28 days of first puncture and puncture a maximum of 10 times.

Intervet Inc. (d/b/a Merck Animal Health)
Rahway, NJ 07065

Formulated in Germany.

Rev. 12/2025

Copyright © 2025 Merck & Co., Inc., Rahway, NJ,
USA and its affiliates.
All rights reserved.

MERCK
Animal Health

244432 R1

PRINCIPAL DISPLAY PANEL - 100 mL Vial Label

100 mg/mL

Sterile

Garasol®
(gentamicin injection)
Injection

Caution: Federal law restricts
this drug to use by or on the
order of a licensed veterinarian

(100 mL)

Approved by FDA under
NADA # 101-862

MERCK
Animal Health